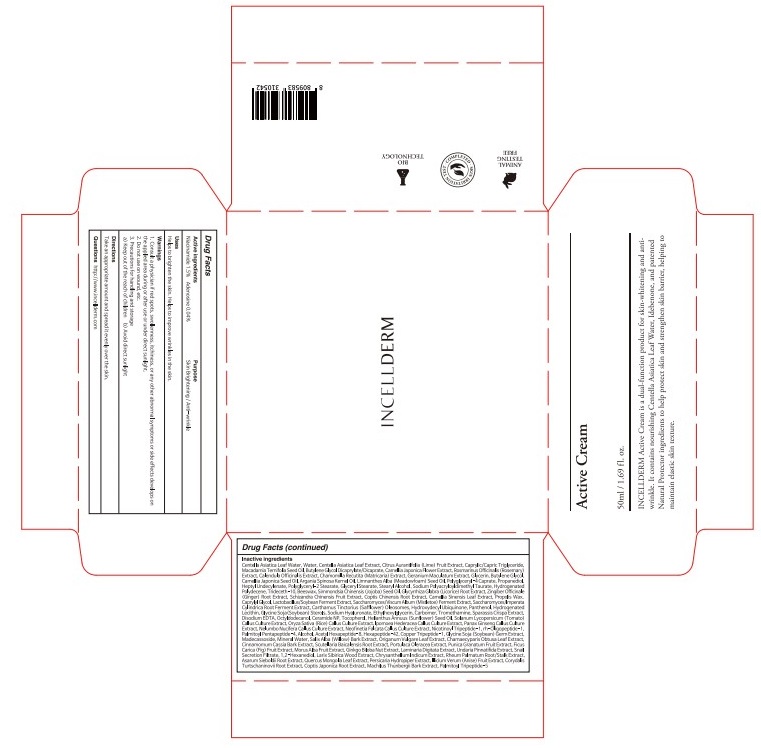 DRUG LABEL: INCELLDERM ACTIVE
NDC: 72650-010 | Form: CREAM
Manufacturer: Riman Co., Ltd.
Category: otc | Type: HUMAN OTC DRUG LABEL
Date: 20200820

ACTIVE INGREDIENTS: Niacinamide 0.75 g/50 mL; Adenosine 0.02 g/50 mL
INACTIVE INGREDIENTS: CENTELLA ASIATICA LEAF; WATER

ACTIVE INGREDIENTS

Niacinamide 1.5%

Adenosine 0.04%

INACTIVE INGREDIENTS

Centella Asiatica Leaf Water, Water, Centella Asiatica Leaf Extract, Citrus Aurantlfolia (Lime) Fruit Extract, Caprylic/Capric Triglyceride, Macadamia Ternifolia Seed Oil, Butylene Glycol Dicaprylate/Dicaprate, Camellia Japonica Flower Extract, Rosmarinus Officinalis (Rosemary) Extract, Calendula
Officinalis Extract, Chamomilla Recutita (Matricaria) Extract, Geranium Maculatum Extract, Glycerin, Butylene Glycol, Camellia Japonica Seed Oil, Argania Spinosa Kernel Oil, Limnanthes Alba (Meadowfoam) Seed Oil, Polyglyceryl-4 Caprate, Propanediol, Heptyl Undecylenate, Polyglyceryl-2 Stearate, Glyceryl Stearate, Stearyl Alcohol, Sodium Polyacryloyldimethyl Taurate, Hydrogenated Polydecene, Trideceth-10, Beeswax, Simmondsia Chinensis (Jojoba) Seed Oil, Glycyrrhiza Glabra (Licorice) Root Extract, Zingiber Officinale (Ginger) Root Extract, Schizandra Chinensis Fruit Extract, Coptis Chinensis Root Extract, Camellia Sinensis Leaf Extract, Propolis Wax, Caprylyl Glycol, Lactobacillus/Soybean Ferment Extract, Saccharomyces/Viscum Album (Mistletoe) Ferment Extract, Saccharomyces/Imperata Cylindrica Root Ferment Extract, Carthamus Tinctorius (Safflower) Oleosomes, Hydroxydecyl Ubiquinone, Panthenol, Hydrogenated Lecithin, Glycine Soja(Soybean) Sterols, Sodium Hyaluronate, Ethylhexylglycerin, Carbomer, Tromethamine, Sparassis Crispa Extract, Disodium EDTA, Octyldodecanol, Ceramide NP, Tocopherol, Helianthus Annuus (Sunflower) Seed Oil, Solanum Lycopersicum (Tomato) Callus Culture Extract, Oryza Sativa (Rice) Callus Culture Extract, Ipomoea Hederacea Callus Culture Extract, Panax Ginseng Callus Culture Extract, Nelumbo Nucifera Callus Culture Extract, Neofinetia Falcata Callus Culture Extract, Nicotinoyl Tripeptide-1, rh-Oligopeptide-1, Palmitoyl Pentapeptide-4, Alcohol, Acetyl Hexapeptide-8, Hexapeptide-42, Copper Tripeptide-1, Glycine Soja (Soybean) Germ Extract, Madecassoside, Mineral Water, Salix Alba (Willow) Bark Extract, Origanum Vulgare Leaf Extract, Chamaecyparis Obtusa Leaf Extract, Cinnamomum Cassia Bark Extract, Scutellaria Baicalensis Root Extract, Portulaca Oleracea Extract, Punica Granatum Fruit Extract, Ficus Carica (Fig) Fruit Extract, Morus Alba Fruit Extract, Ginkgo Biloba Nut Extract, Laminaria Digitata Extract, Undaria Pinnatifida Extract, Snail Secretion Filtrate, 1,2-Hexanediol, Larix Sibirica Wood Extract, Chrysanthellum Indicum Extract, Rheum Palmatum Root/Stalk Extract, Asarum Sieboldii Root Extract, Quercus Mongolia Leaf Extract, Persicaria Hydropiper Extract, Illicium Verum (Anise) Fruit Extract, Corydalis Turtschaninovii Root Extract, Coptis Japonica Root Extract, Machilus Thunbergii Bark Extract, Palmitoyl Tripeptide-5

PURPOSE

Skin Brightening

Anti-wrinkle

WARNINGS

1. Consult a physician if red spots, swollenness, itchiness, or any other abnormal symptoms or side effects develops on the applied area during or after use or under direct sunlight.
2. Do not use on wound, etc.
3. Precautions for handling and storage
a) Keep out of the reach of children
b) Avoid direct sunlight

KEEP OUT OF REACH OF CHILDREN

Uses

Helps to brighten the skin.
Helps to improve wrinkles in the skin.

Directions

Take an appropriate amount and spread it evenly over the skin.
Please put the appropriate amount on the skin and wait (daub).